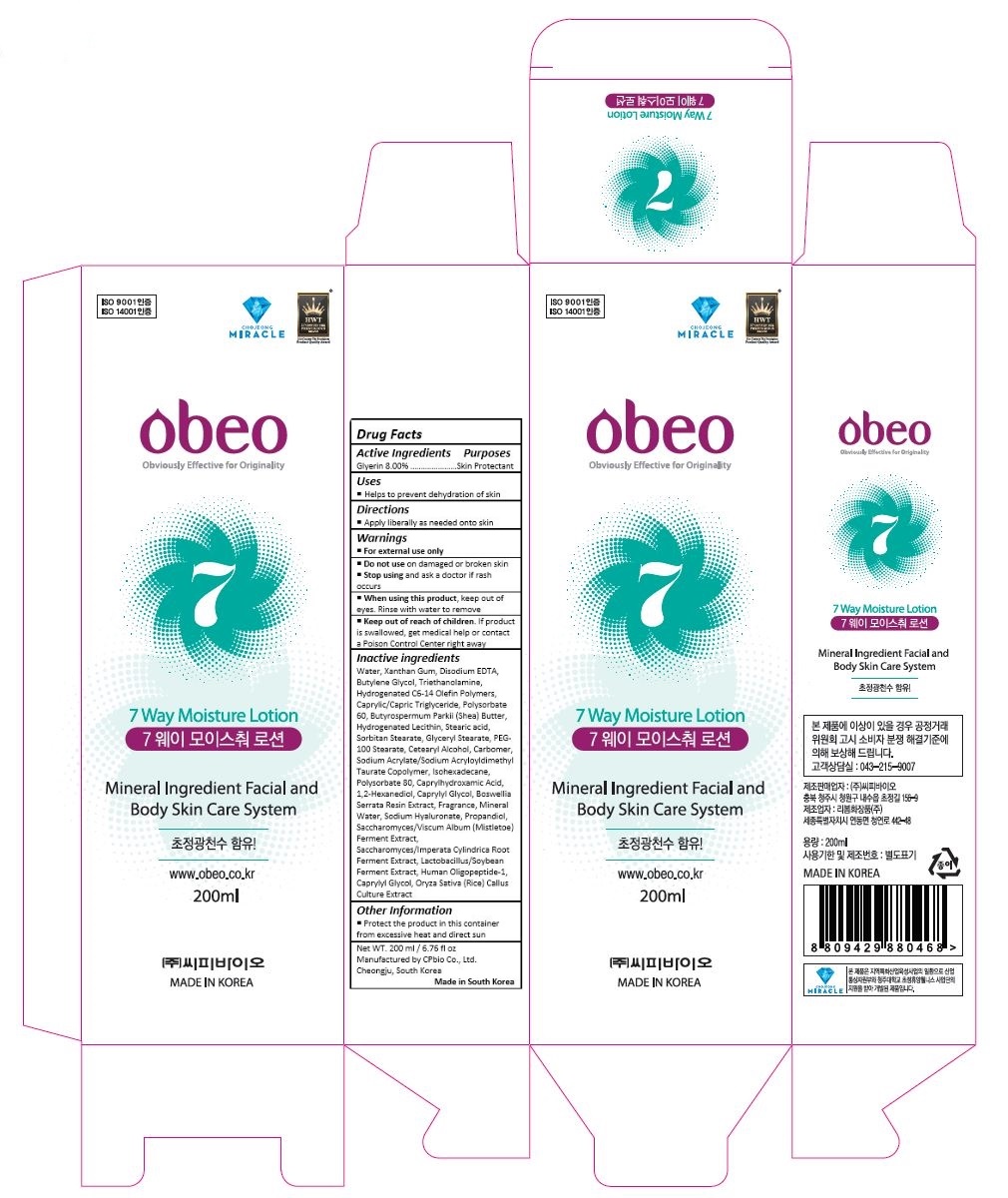 DRUG LABEL: Obeo 7way Moisture
NDC: 69871-003 | Form: LOTION
Manufacturer: CPbio Co., Ltd
Category: otc | Type: HUMAN OTC DRUG LABEL
Date: 20160125

ACTIVE INGREDIENTS: GLYCERIN 16 mg/200 mL
INACTIVE INGREDIENTS: WATER; XANTHAN GUM; EDETATE DISODIUM; BUTYLENE GLYCOL; TROLAMINE; MEDIUM-CHAIN TRIGLYCERIDES; POLYSORBATE 60; SHEA BUTTER; HYDROGENATED SOYBEAN LECITHIN; STEARIC ACID; GLYCERYL MONOSTEARATE; PEG-100 STEARATE; CETOSTEARYL ALCOHOL; CARBOXYPOLYMETHYLENE; SODIUM ACRYLATE/SODIUM ACRYLOYLDIMETHYLTAURATE COPOLYMER (4000000 MW); ISOHEXADECANE; POLYSORBATE 80; CAPRYLHYDROXAMIC ACID; 1,2-HEXANEDIOL; CAPRYLYL GLYCOL; INDIAN FRANKINCENSE; HYALURONATE SODIUM; PROPANEDIOL; VISCUM ALBUM FRUITING TOP; IMPERATA CYLINDRICA ROOT

Drug Facts

ACTIVE INGREDIENT

Glyerin 8.00%

PURPOSE

Skin Protectant

INDICATIONS AND USAGE

Helps to prevent dehydration of skin

DOSAGE AND ADMINISTRATION

Apply liberally as needed onto skin

WARNINGS

For external use only

Do not use on damaged or broken skin

Stop using and ask a doctor if rash occurs

When using this product, keep out of eyes. Rinse with water to remove

Keep out of reach of children. If product is swallowed, get medical help or contact a Poison Control Center right away.

INACTIVE INGREDIENT

Water, Xanthan Gum, Disodium EDTA, Butylene Glycol, Triethanolamine, Hydrogenated C6-14 Olefin Polymers, Caprylic/Capric Triglyceride, Polysorbate 60, Butyrospermum Parkii (Shea) Butter, Hydrogenated Lecithin, Stearic acid, Sorbitan Stearate, Glyceryl Stearate, PEG-100 Stearate, Cetearyl Alcohol, Carbomer, Sodium Acrylate/Sodium Acryloyldimethyl Taurate Copolymer, Isohexadecane, Polysorbate 80, Caprylhydroxamic Acid, 1,2-Hexanediol, Caprylyl Glycol, Boswellia Serrata Resin Extract, Fragrance, Mineral Water, Sodium Hyaluronate, Propandiol, Saccharomyces/Viscum Album (Mistletoe) Ferment Extract, Saccharomyces/Imperata Cylindrica Root Ferment Extract, Lactobacillus/Soybean Ferment Extract, Human Oligopeptide-1, Caprylyl Glycol, Oryza Sativa (Rice) Callus Culture Extract